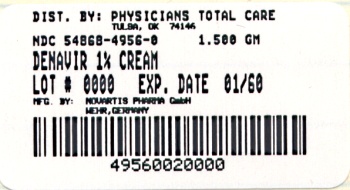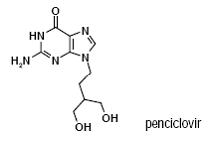 DRUG LABEL: Denavir
NDC: 54868-4956 | Form: CREAM
Manufacturer: Physicians Total Care, Inc.
Category: prescription | Type: HUMAN PRESCRIPTION DRUG LABEL
Date: 20091001

ACTIVE INGREDIENTS: PENCICLOVIR 10 mg/1 g
INACTIVE INGREDIENTS: CETETH-20; CETOSTEARYL ALCOHOL; MINERAL OIL; PROPYLENE GLYCOL; WATER; PETROLATUM

Denavir

Denavir® brand ofpenciclovir cream, 1%

For Dermatologic Use Only

Rx Only

Prescribing Information

DESCRIPTION

Denavir contains penciclovir, an antiviral agent active against herpes viruses. Denavir is available for topical administration as a 1% white cream. Each gram of Denavir contains 10 mg of penciclovir and the following inactive ingredients: cetomacrogol 1000 BP, cetostearyl alcohol, mineral oil, propylene glycol, purified water and white petrolatum. Chemically, penciclovir is known as 9-[4-hydroxy-3-(hydroxymethyl) butyl]guanine. Its molecular formula is C10H15N5O3; its molecular weight is 253.26. It is a synthetic acyclic guanine derivative and has the following structure:

Penciclovir is a white to pale yellow solid. At 20°C it has a solubility of 0.2 mg/mL in methanol, 1.3 mg/mL in propylene glycol, and 1.7 mg/mL in water. In aqueous buffer (pH 2) the solubility is 10.0 mg/mL. Penciclovir is not hygroscopic. Its partition coefficient in n-octanol/water at pH 7.5 is 0.024 (logP= -1.62).

CLINICAL PHARMACOLOGY

Microbiology

Mechanism of Antiviral Activity: The antiviral compound penciclovir has in vitro inhibitory activity against herpes simplex virus types 1 (HSV-1) and 2 (HSV-2). In cells infected with HSV-1 or HSV-2, viral thymidine kinase phosphorylates penciclovir to a monophosphate form which, in turn, is converted to penciclovir triphosphate by cellular kinases. In vitro studies demonstrate that penciclovir triphosphate inhibits HSV polymerase competitively with deoxyguanosine triphosphate. Consequently, herpes viral DNA synthesis and, therefore, replication are selectively inhibited.

Antiviral Activity In Vitro and In Vivo: In cell culture studies, penciclovir has antiviral activity against HSV-1 and HSV-2. Sensitivity test results, expressed as the concentration of the drug required to inhibit growth of the virus by 50% (IC50) or 99% (IC99) in cell culture, vary depending upon a number of factors, including the assay protocols. See Table 1.

Table 1

Method of Assay | Virus Type | Cell Type | IC 50 (mcg/mL) | IC 99 (mcg/mL)
Plaque Reduction | HSV-1 (c.i.) | MRC-5 | 0.2-0.6
Plaque Reduction | HSV-1 (c.i.) | WISH | 0.04-0.5
Plaque Reduction | HSV-2 (c.i.) | MRC-5 | 0.9-2.1
Plaque Reduction | HSV-2 (c.i.) | WISH | 0.1-0.8
Virus Yield Reduction | HSV-1 (c.i.) | MRC-5 |  | 0.4-0.5
Virus Yield Reduction | HSV-2 (c.i.) | MRC-5 |  | 0.6-0.7
DNA Synthesis Inhibition | HSV-1 (SC16) | MRC-5 | 0.04
DNA Synthesis Inhibition | HSV-2 (MS) | MRC-5 | 0.05

(c.i.) = clinical isolates. The latent state of any herpes virus is not known to respond to any antiviral therapy.

Drug Resistance: Penciclovir-resistant mutants of HSV can result from qualitative changes in viral thymidine kinase or DNA polymerase. The most commonly encountered acyclovir resistant mutants that are deficient in viral thymidine kinase are also resistant to penciclovir.

Pharmacokinetics

Measurable penciclovir concentrations were not detected in plasma or urine of healthy male volunteers (n=12) following single or repeat application of the 1% cream at a dose of 180 mg penciclovir daily (approximately 67 times the estimated usual clinical dose). Pediatric Patients: The systemic absorption of penciclovir following topical administration has not been evaluated in patients <18 years of age.

CLINICAL TRIALS

Denavir was studied in two double-blind, placebo (vehicle)-controlled trials for the treatment of recurrent herpes labialis in which otherwise healthy adults were randomized to either Denavir or placebo. Therapy was to be initiated by the subjects within 1 hour of noticing signs or symptoms and continued for 4 days, with application of study medication every 2 hours while awake. In both studies, the mean duration of lesions was approximately one-half-day shorter in the subjects treated with Denavir (N=1,516) as compared to subjects treated with placebo (N=1,541) (approximately 4.5 days versus 5 days, respectively). The mean duration of lesion pain was also approximately one-half-day shorter in the Denavir group compared to the placebo group.

INDICATIONS AND USAGE

Denavir (penciclovir cream) is indicated for the treatment of recurrent herpes labialis (cold sores) in adults and children 12 years of age and older.

CONTRAINDICATIONS

Denavir is contraindicated in patients with known hypersensitivity to the product or any of its components.

PRECAUTIONS

General

Denavir should only be used on herpes labialis on the lips and face. Because no data are available, application to human mucous membranes is not recommended. Particular care should be taken to avoid application in or near the eyes since it may cause irritation. Lesions that do not improve or that worsen on therapy should be evaluated for secondary bacterial infection. The effect of Denavir has not been established in immuno-compromised patients.

Information for Patients

Denavir is a prescription topical cream for the treatment of cold sores (recurrent herpes labialis) that occur on the face and lips. It is not a cure for cold sores and not all patients respond to it. Do not use if you are allergic to Denavir (penciclovir) or any of the ngredients in Denavir cream. Before you use Denavir, tell your doctor if you are pregnant, planning to become pregnant, or are breast-feeding.

Directions: Wash your hands. Your face should be clean and dry. Apply a layer of Denavir cream to cover only the cold sore area or the area of tingling (or other symptoms) before the cold sore appears. Rub in the cream until it disappears. Apply the cream every 2 hours during waking hours for 4 days. Even though Denavir works at the blister stage, treatment should be started at the earliest sign of a cold sore (i.e. tingling, redness, itching, or bump). Wash your hands with soap and water after using Denavir cream. Store Denavir cream at room temperature (59°-86°F). Keep out of reach of children.

Possible side effects: Denavir cream was well tolerated in clinical studies in patients with cold sores. The most frequently reported side effect was headache. Common skin-related side effects of Denavir cream are application site reactions, local anesthesia, taste perversion, and rash.

Carcinogenesis, Mutagenesis, Impairment of Fertility

In clinical trials, systemic drug exposure following the topical administration of penciclovir cream was negligible, as the penciclovir content of all plasma and urine samples was below the limit of assay detection (0.1 mcg/mL and 10 mcg/mL, respectively). However, for the purpose of inter-species dose comparisons presented in the following sections, an assumption of 100% absorption of penciclovir from the topically applied product has been used. Based on use of the maximal recommended topical dose of penciclovir of 0.05 mg/kg/day and an assumption of 100% absorption, the maximum theoretical plasma AUC0-24 hrs for penciclovir is approximately 0.129 mcg.hr/mL.

Carcinogenesis: Two-year carcinogenicity studies were conducted with famciclovir (the oral prodrug of penciclovir) in rats and mice. An increase in the incidence of mammary adenocarcinoma (a common tumor in female rats of the strain used) was seen in female rats receiving 600 mg/kg/day (approximately 395x the maximum theoretical human exposure to penciclovir following application of the topical product, based on area under the plasma concentration curve comparisons [24 hr. AUC]). No increases in tumor incidence were seen among male rats treated at doses up to 240 mg/kg/day (approximately 190x the maximum theoretical human AUC for penciclovir), or in male and female mice at doses up to 600 mg/kg/day (approximately 100x the maximum theoretical human AUC for penciclovir).

Mutagenesis: When tested in vitro, penciclovir did not cause an increase in gene mutation in the Ames assay using multiple strains of S. typhimurium or E. coli (at up to 20,000 mcg/plate), nor did it cause an increase in unscheduled DNA repair in mammalian HeLa S3 cells (at up to 5,000 mcg/mL). However, an increase in clastogenic responses was seen with penciclovir in the L5178Y mouse lymphoma cell assay (at doses ≥1000 mcg/mL) and, in human lymphocytes incubated in vitro at doses ≥ 250 mcg/mL. When tested in vivo, penciclovir caused an increase in micronuclei in mouse bone marrow following the intravenous administration of doses ≥ 500 mg/kg (≥ 810x the maximum human dose, based on body surface area conversion).

Impairment of Fertility: Testicular toxicity was observed in multiple animal species (rats and dogs) following repeated intravenous administration of penciclovir (160 mg/kg/day and 100 mg/kg/day, respectively, approximately 1155 and 3255x the maximum theoretical human AUC). Testicular changes seen in both species included atrophy of the seminiferous tubules and reductions in epididymal sperm counts and/or an increased incidence of sperm with abnormal morphology or reduced motility. Adverse testicular effects were related to an increasing dose or duration of exposure to penciclovir. No adverse testicular or reproductive effects (fertility and reproductive function) were observed in rats after 10 to 13 weeks dosing at 80 mg/kg/day, or testicular effects in dogs after 13 weeks dosing at 30 mg/kg/day (575 and 845x the maximum theoretical human AUC, respectively). Intravenously administered penciclovir had no effect on fertility or reproductive performance in female rats at doses of up to 80 mg/kg/day (260x the maximum human dose [BSA]).

There was no evidence of any clinically significant effects on sperm count, motility or morphology in 2 placebo-controlled clinical trials of Famvir® (famciclovir [the oral prodrug of penciclovir], 250 mg b.i.d.; n=66) in immunocompetent men with recurrent genital herpes, when dosing and follow-up were maintained for 18 and 8 weeks, respectively (approximately 2 and 1 spermatogenic cycles in the human).

Pregnancy

Teratogenic Effects-Pregnancy Category B. No adverse effects on the course and outcome of pregnancy or on fetal development were noted in rats and rabbits following the intravenous administration of penciclovir at doses of 80 and 60 mg/kg/day, respectively (estimated human equivalent doses of 13 and 18 mg/kg/day for the rat and rabbit, respectively, based on body surface area conversion; the body surface area doses being 260 and 355x the maximum recommended dose following topical application of the penciclovir cream). There are, however, no adequate and well-controlled studies in pregnant women. Because animal reproduction studies are not always predictive of human response, penciclovir should be used during pregnancy only if clearly needed.

Nursing Mothers

There is no information on whether penciclovir is excreted in human milk after topical administration. However, following oral administration of famciclovir (the oral prodrug of penciclovir) to lactating rats, penciclovir was excreted in breast milk at concentrations higher than those seen in the plasma. Therefore, a decision should be made whether to discontinue the drug, taking into account the importance of the drug to the mother. There

are no data on the safety of penciclovir in newborns.

Pediatric Use

An open-label, uncontrolled trial with penciclovir cream 1% was conducted in 102 patients, ages 12-17 years, with recurrent herpes labialis. The frequency of adverse events was generally similar to the frequency previously reported for adult patients. Safety and effectiveness in pediatric patients less than 12 years of age have not been established.

Geriatric Use

In 74 patients ≥ 65 years of age, the adverse events profile was comparable to that observed in younger patients.

ADVERSE REACTIONS

In two double-blind, placebo-controlled trials, 1516 patients were treated with Denavir (penciclovir cream) and 1541 with placebo. The most frequently reported adverse event was headache, which occurred in 5.3% of the patients treated with Denavir and 5.8% of the placebo-treated patients. The rates of reported local adverse reactions are shown in Table 2 below. One or more local adverse reactions were reported by 2.7% of the patients treated with Denavir and 3.9% of placebotreated patients.

Table 2--Local Adverse Reactions Reported in Phase III Trials

 | Penciclovir n=1516 % | Placebo n=1541 %
Application site reaction | 1.3 | 1.8
Hypesthesia/Local anesthesia | 0.9 | 1.4
Taste pervesion | 0.2 | 0.3
Puritus | 0 | 0.3
Pain | 0 | 0.1
Rash (erthematous) | 0.1 | 0.1
Allergic reaction | 0 | 0.1

Two studies, enrolling 108 healthy subjects, were conducted to evaluate the dermal tolerance of 5% penciclovir cream (a 5-fold higher concentration than the commercial formulation) compared to vehicle using repeated occluded patch testing methodology. The 5% penciclovir cream induced mild erythema in approximately one-half of the subjects exposed, an irritancy profile similar to the vehicle control in terms of severity and proportion of subjects with a response. No evidence of sensitization was observed.

Post-Marketing Experience

The following events have been identified from worldwide post-marketing use of Denavir in treatment of recurrent herpes labialis (cold sores) in adults. These events have been chosen for inclusion due to a combination of their seriousness, frequency of reporting, or potential causal connection to Denavir cream.

General: Headache, oral/pharyngeal edema, parosmia.

Skin: Application site reactions, aggravated condition, decreased therapeutic response, erythematous rash, local edema, pain, paresthesia, pruritus, skin discoloration and urticaria.

OVERDOSAGE

Since penciclovir is poorly absorbed following oral administration, adverse reactions related to penciclovir ingestion are unlikely. There is no information on overdose.

DOSAGE AND ADMINISTRATION

Denavir should be applied every 2 hours during waking hours for a period of 4 days. Treatment should be started as early as possible (i.e., during the prodrome or when lesions appear).

HOW SUPPLIED

Denavir is supplied in a 1.5 gram tube containing 10mg of penciclovir per gram.

NDC 54868-4956-0

Store at controlled room temperature, 20°-25° C (68°-77°F) [see USP]

QUESTIONS? call 1-800-452-0051 24 hours a day, 7 days a week.

October 2003

Manufactured by Novartis Pharma GmbH,

Wehr, Germany for

Novartis Consumer Health, Inc.

Parsippany, NJ 07054-0622

©2004 Novartis Consumer Health, Inc.

Relabeling of "Additional" barcode label by:
Physicians Total Care, Inc.
Tulsa, OK 74146

PRINCIPAL DISPLAY PANEL

Denavir
1.5 gram